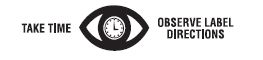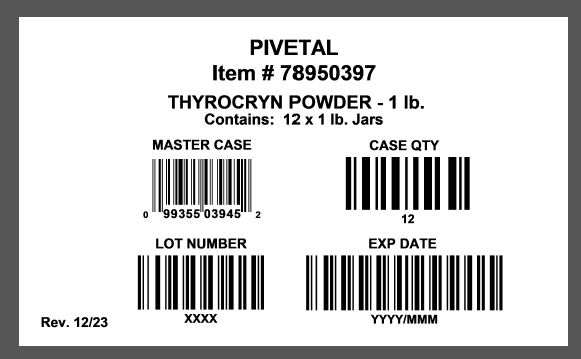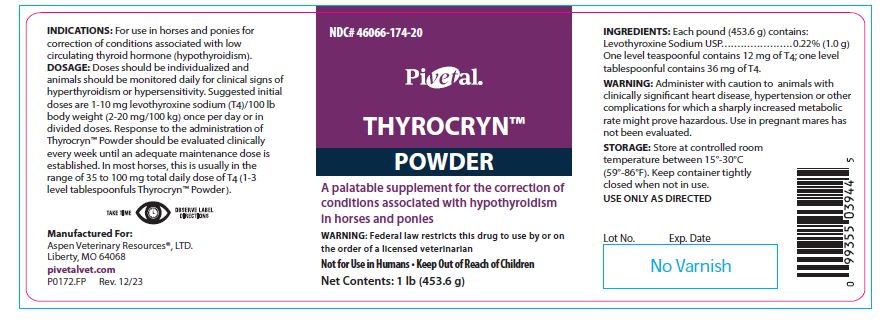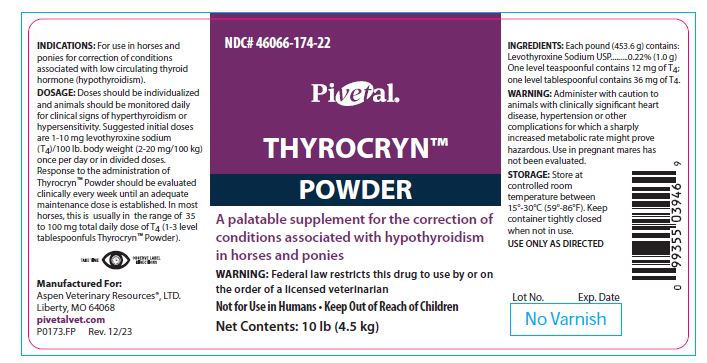 DRUG LABEL: THYROCRYN
NDC: 46066-174 | Form: POWDER
Manufacturer: Aspen Veterinary Resources
Category: animal | Type: PRESCRIPTION ANIMAL DRUG LABEL
Date: 20240227

ACTIVE INGREDIENTS: LEVOTHYROXINE SODIUM 1000 mg/453.6 g

THYROCRYN™
POWDER

INFORMATION FOR OWNERS/CAREGIVERS

A palatable supplement for the correction of conditions associated with hypothyroidism in horses and ponies

WARNINGS AND PRECAUTIONS

WARNING: Federal law restricts this drug to use by or on the order of a licensed veterinarian

Not for Use in Humans • Keep Out of Reach of Children

INDICATIONS:

For use in horses and ponies for correction of conditions associated with low circulating thyroid hormone (hypothyrodism).

DOSAGE:

Doses should be individualized and animals should be monitored daily for clinical signs of hyperthyroidism or hypersensitivity. Suggested initial doses are 1-10 mg levothyroxine sodium (T4)/100 lb body weight (2-20 mg/100 kg) once per day or in divided doses. Response to the administration of Thyrocryn™ Powder should be evaluated clinically every week until an adequate maintenance dose is established. In most horses, this is usually in the range of 35 to 100 mg total daily dose of T4 (1-3 level tablespoonfuls Thyrocryn™ Powder).

INGREDIENTS:

Each pound (453.6 g) contains:

Levothyroxine Sodium USP ........................................ 0.22% (1.0 g)

One level teaspoonful contains 12 mg of T4: one level tablespoonful contains 36 mg of T4.

WARNING:

Administer with caution to animals with clincially significant heart disease, hypertension or other complications for which a sharply increased metabolic rate might prove hazardous. Use in pregnant mares has not been evaluated.

STORAGE AND HANDLING

STORAGE: Store at controlled room temperature between 15° - 30°C (59° - 86°F). Keep container tightly closed when not in use.

USE ONLY AS DIRECTED

HOW SUPPLIED

Net Contents:

1 lb (453.6 grams), P0172.FP

10 lb (4.5 kg), P0173.FP